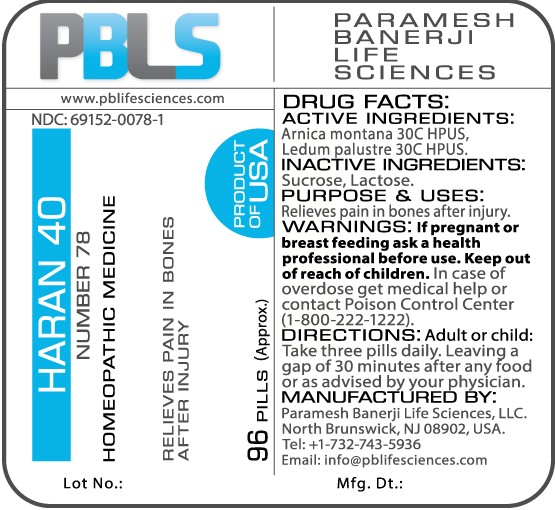 DRUG LABEL: Haran 40 (Number 78)
NDC: 69152-0078 | Form: PELLET
Manufacturer: Paramesh Banerji Life Sciences LLC
Category: homeopathic | Type: HUMAN OTC DRUG LABEL
Date: 20161226

ACTIVE INGREDIENTS: ARNICA MONTANA 30 [hp_C]/1 1; LEDUM PALUSTRE TWIG 30 [hp_C]/1 1
INACTIVE INGREDIENTS: SUCROSE; LACTOSE

Drug Facts: Active Ingredients

Arnica montana 30C HPUS, Ledum palustre 30C HPUS

Inactive Ingredients

Sucrose, Lactose

Purpose

Relieves pain in bones after injury

Uses

Relieves pain in bones after injury

Warnings

If pregnant or breast feeding ask a health professional before use.

Keep out of reach of children. In case of overdose, get medical help or contact a Poison Control Center (1-800-222-1222) right away.

Direction

Adult or child: Take three pills daily. Leaving a gap of 30 minutes after any food or as advised by your physician.

Manufactured by

Paramesh Banerji Life Sciences, LLC.

North Brunswick, NJ 08902, USA.

Tel: +1-732-743-5936

Email: info@pblifesciences.com

Principal Display Panel

NDC: 69152-0078-1

Haran 40

Number 78

Homeopathic Medicine

Relieves pain in bones after injury

96 Pills (Approx.)

Product of USA